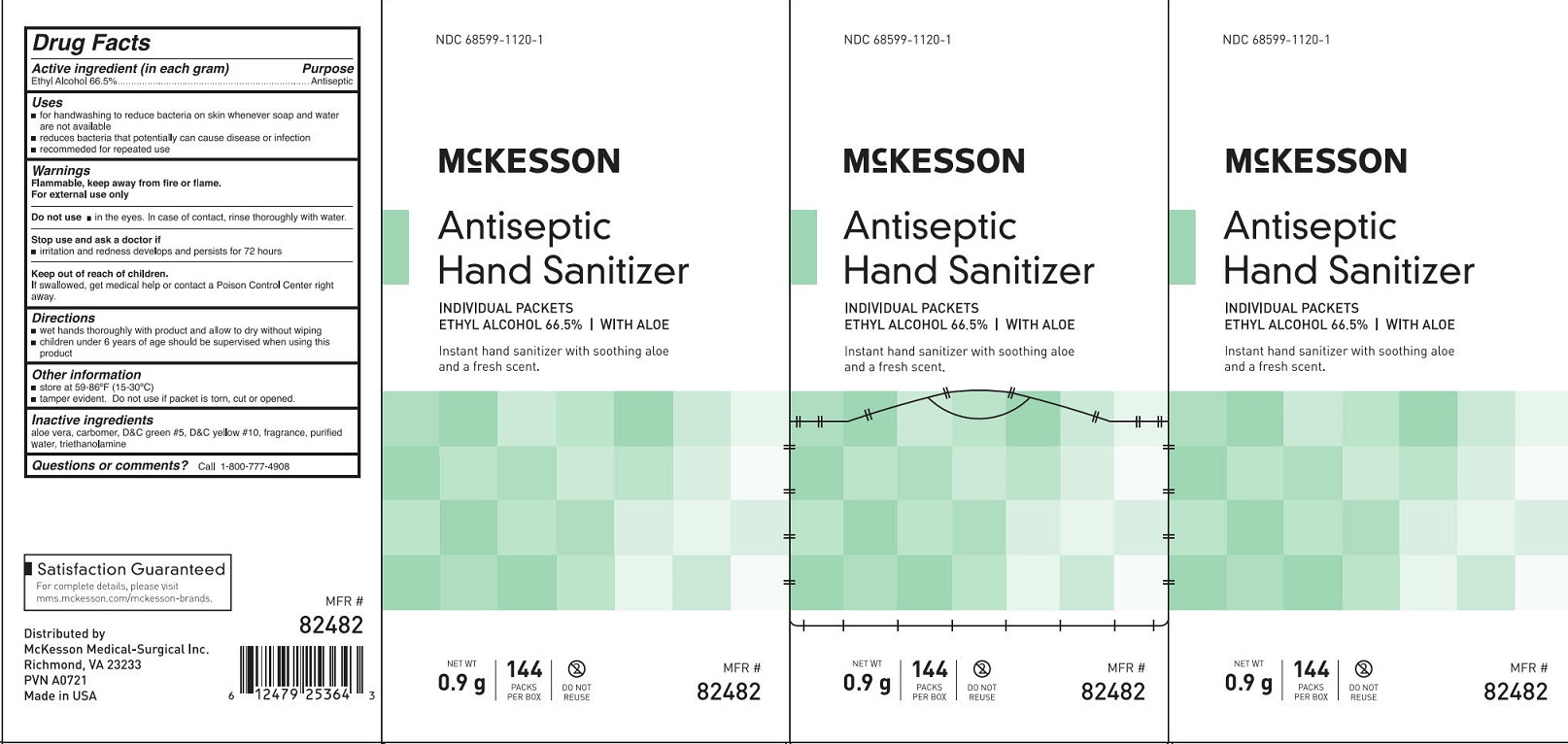 DRUG LABEL: McKesson Antiseptic Hand Sanitizer
NDC: 68599-1120 | Form: GEL
Manufacturer: McKesson Medical-Surgical
Category: otc | Type: HUMAN OTC DRUG LABEL
Date: 20250909

ACTIVE INGREDIENTS: ALCOHOL 665 g/1 L
INACTIVE INGREDIENTS: WATER; ALOE; TROLAMINE; D&C GREEN NO. 5; CARBOMER INTERPOLYMER TYPE A (ALLYL SUCROSE CROSSLINKED); D&C YELLOW NO. 10

McKesson Antiseptic Hand Sanitizer

Drug Facts

Active ingredient (in each gram)

Ethyl Alcohol 66.5%

Purpose

Antiseptic

Uses

- for handwashing to reduce bacteria on skin whenever soap and water are not available
- reduces bacteria that potentially can cause disease or infection
- recommended for repeated use

Warnings

Flammable. keep away from fire of flame.

For external use only

Do not use

- in the eyes. In case of contact, rinse thoroughly with water.

Stop use and ask a doctor if

- irritation and redness develops and persist for 72 hours

Keep out of reach of children.

If swallowed, get medical help or contact a Poison Control Center right away.

Directions

- wet hands thoroughly with product and allow to dry without wiping
- children under 6 years of age should be supervised while using this product

Other information

- store at 59-86ºF (15-30ºC)
- tamper evident. Do not use if packet is torn, cut or opened.

Inactive ingredients

aloe vera, carbomer, DD&C green #5, D&C yellow #10, fragrance, purified water, triethanolamine

Questions or comments? Call 1-800-777-4908

PACKAGE LABEL

NDC 68599-1120-1

McKesson

Antiseptic Hand Sanitizer

Individual Packets

Ethyl Alcohol 66.5% | With Aloe

Instant hand sanitizer with soothing aloe and a fresh scent.

NET WT 0.9 g

144 Packs Per Box

Do Not Reuse

MFR # 82482